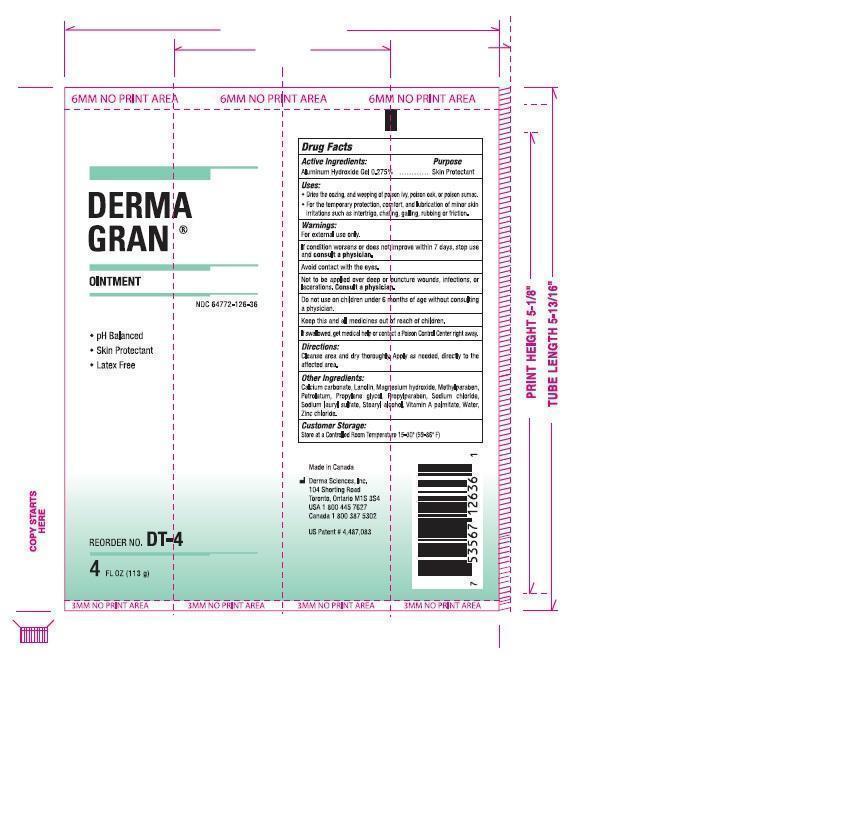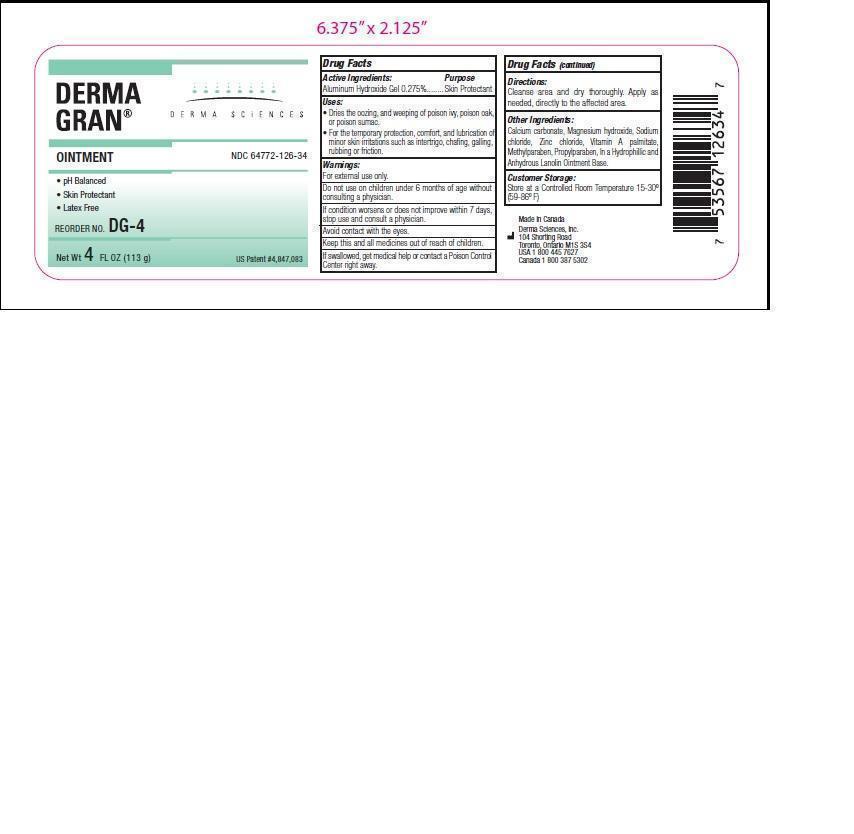 DRUG LABEL: DERMA GRAN
                
                        
NDC: 64772-126 | Form: OINTMENT
Manufacturer: Derma Sciences Canada, Inc.
Category: otc | Type: HUMAN OTC DRUG LABEL
Date: 20150616

ACTIVE INGREDIENTS: ALGELDRATE 0.275 g/100 g
INACTIVE INGREDIENTS: CALCIUM CARBONATE; LANOLIN; MAGNESIUM HYDROXIDE; METHYLPARABEN; PETROLATUM; PROPYLENE GLYCOL; PROPYLPARABEN; SODIUM CHLORIDE; SODIUM LAURYL SULFATE; STEARYL ALCOHOL; VITAMIN A PALMITATE; WATER; ZINC CHLORIDE

Drug Facts

Active Ingredients:

Aluminium Hydroxide Gel 0.275%

Purpose

Skin Protectant

Uses:

- Dries the oozing, and weeping of poison ivy, poison oak, or poison sumac.
- For the temporary protection, comfort and lubrication of minor skin irritations such as intertrigo, chafing, galling, rubbing or friction.

Warnings:

For external use only.

Avoid contact with eyes.

Not to be applied over deep or puncture wounds, infections or lacerations. Consult a physician.

STOP USE

If condition worsens or does not improve within 7 days stop use and consult a physician.

Do not use on

children under 6 months of age without consulting a physician.

Keep this and all medicines out of reach of children.

If swallowed, get medical help or contact a Poison Control Center right away.

Directions

Cleanse area and dry thoroughly. Apply as needed, directly to the affected area.

Other Ingredients:

Calcium carbonate, Lanolin, Magnesium hydroxide, Methlyparaben, Petrolatum, Propylene glycol, Propylparaben, Sodium Chloride, Sodium Lauryl Sulfate, Stearyl alcohol, Vitamin A Palmitate, Water, Zinc Chloride.

Customer Storage:

Store at a Controlled Room Temperature 15-30o(59-86oF)

Principal Display Panel

DERMA GRAN

OINTMENT

NDC 64772-126-36

- pH Balanced
- Skin Protectant
- Latex Free

4 FL OZ (113 g)

DERMA GRAN

OINTMENT

NDC 64771-126-34

- pH Balanced
- Skin Protectant
- Latex Free